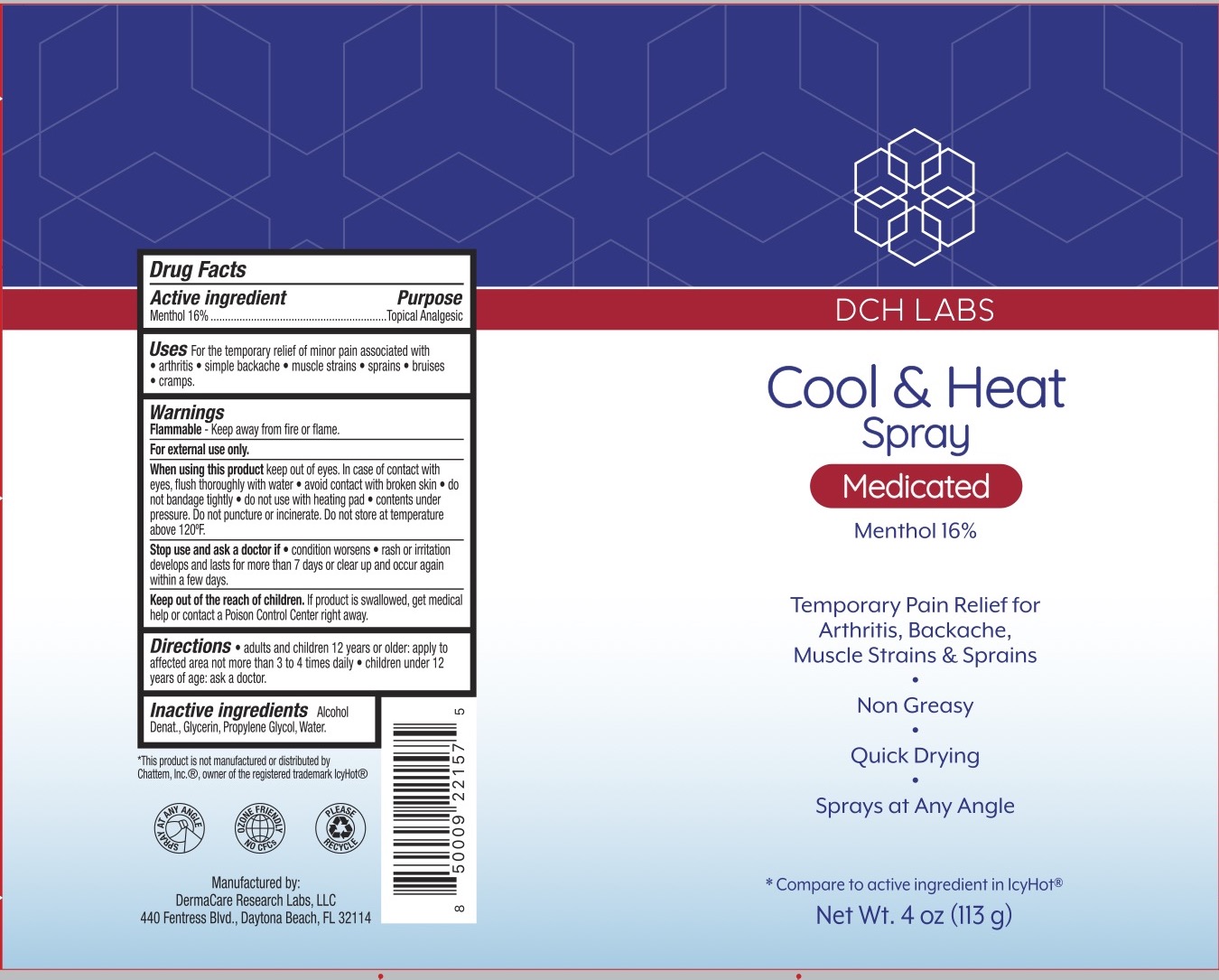 DRUG LABEL: DCH Cool and Heat
NDC: 72839-129 | Form: SPRAY
Manufacturer: Derma Care Research Labs, LLC
Category: otc | Type: HUMAN OTC DRUG LABEL
Date: 20250127

ACTIVE INGREDIENTS: MENTHOL 16 g/100 g
INACTIVE INGREDIENTS: PROPYLENE GLYCOL; WATER; GLYCERIN; ALCOHOL

DCH Cool and Heat Spray, 16% Menthol

ACTIVE INGREDIENT

Menthol 16%

PURPOSE

Topical Analgesic

INDICATIONS AND USAGE

For the temporary relief of minor aches and pain associated with arthritis, simple backache, muscle strains, bruises, and sprains.

WARNINGS

For external use only. Flammable--Keep away from fire or flame. When using this product avoid contact with eyes. In case of contact with eyes, flush thoroughly with water, do not apply to wounds or damaged skin, and do not bandage tightly, do not use with a heating pad. Contents under pressure. Do not puncture or incinerate. Do not store at temperature above 120F. . Stop use and ask a doctor if condition worsens, if symptoms persist for more than 7 days or clear up and occur again within a few days.

KEEP OUT OF REACH OF CHILDREN

If swallowed, get medical help or contact a Poison Control Center right away.

DOSAGE AND ADMINISTRATION

Adults and children 12 years of age and older, apply to the affected area not more than 3 to 4 times daily. Children under 12 years of age: ask a doctor.

INACTIVE INGREDIENT

Alcohol Denat., Glycerin, Propylene Glycol, Water